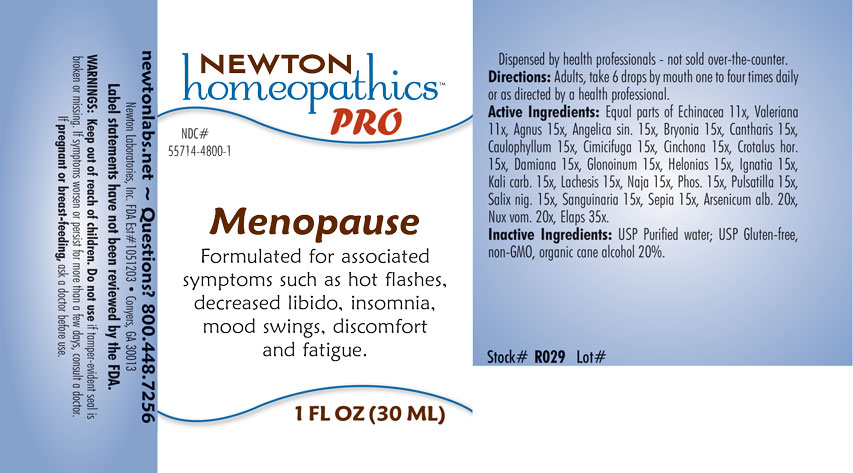 DRUG LABEL: Menopause
NDC: 55714-4800 | Form: LIQUID
Manufacturer: Newton Laboratories, Inc.
Category: homeopathic | Type: HUMAN OTC DRUG LABEL
Date: 20201204

ACTIVE INGREDIENTS: CROTALUS HORRIDUS HORRIDUS VENOM 15 [hp_X]/1 mL; STRYCHNOS IGNATII SEED 15 [hp_X]/1 mL; TURNERA DIFFUSA LEAFY TWIG 15 [hp_X]/1 mL; NITROGLYCERIN 15 [hp_X]/1 mL; CHAMAELIRIUM LUTEUM ROOT 15 [hp_X]/1 mL; POTASSIUM CARBONATE 15 [hp_X]/1 mL; LACHESIS MUTA VENOM 15 [hp_X]/1 mL; NAJA NAJA VENOM 15 [hp_X]/1 mL; STRYCHNOS NUX-VOMICA SEED 20 [hp_X]/1 mL; PHOSPHORUS 15 [hp_X]/1 mL; ANEMONE PULSATILLA 15 [hp_X]/1 mL; SALIX NIGRA BARK 15 [hp_X]/1 mL; SANGUINARIA CANADENSIS ROOT 15 [hp_X]/1 mL; SEPIA OFFICINALIS JUICE 15 [hp_X]/1 mL; ECHINACEA, UNSPECIFIED 11 [hp_X]/1 mL; VALERIAN 11 [hp_X]/1 mL; MICRURUS CORALLINUS VENOM 35 [hp_X]/1 mL; CHASTE TREE FRUIT 15 [hp_X]/1 mL; ANGELICA SINENSIS ROOT 15 [hp_X]/1 mL; ARSENIC TRIOXIDE 20 [hp_X]/1 mL; BRYONIA ALBA ROOT 15 [hp_X]/1 mL; LYTTA VESICATORIA 15 [hp_X]/1 mL; CAULOPHYLLUM THALICTROIDES ROOT 15 [hp_X]/1 mL; BLACK COHOSH 15 [hp_X]/1 mL; CINCHONA OFFICINALIS BARK 15 [hp_X]/1 mL
INACTIVE INGREDIENTS: WATER; ALCOHOL

Menopause 4800L

INDICATIONS & USAGE SECTION

Formulated for associated symptoms such as hot flashes, decreased libido, insomnia, mood swings, discomfort and fatigue.

DOSAGE & ADMINISTRATION SECTION

Directions: Adults, take 6 drops by mouth one to four times daily or as directed by a health professional.

OTC - ACTIVE INGREDIENT SECTION

Equal parts of Echinacea 11x, Valeriana officinalis 11x, Agnus castus 15x, Angelica sinensis radix 15x, Bryonia 15x, Cantharis 15x, Caulophyllum thalictroides 15x, Cimicifuga racemosa 15x, Cinchona officinalis 15x, Crotalus horridus 15x, Damiana 15x, Glonoinum 15x, Helonias dioica 15x, Ignatia amara 15x, Kali carbonicum 15x, Lachesis mutus 15x, Naja tripudians 15x, Phosphorus 15x, Pulsatilla 15x, Salix nigra 15x, Sanguinaria canadensis 15x, Sepia 15x, Arsenicum album 20x, Nux vomica 20x, Elaps corallinus 35x.

OTC - PURPOSE SECTION

Formulated for associated symptoms such as hot flashes, decreased libido, insomnia, mood swings, discomfort and fatigue.

INACTIVE INGREDIENT SECTION

Inactive Ingredients: USP Purified Water; USP Gluten-free, non-GMO, organic cane alcohol 20%.

QUESTIONS SECTION

newtonlabs.net – Questions? 800.448.7256

Newton Laboratories, Inc. FDA Est # 1051203 - Conyers, GA 30013

WARNINGS SECTION

WARNINGS: Keep out of reach of children. Do not use if tamper-evident seal is broken or missing. If symptoms worsen or persist for more than a few days, consult a doctor. If pregnant or breast-feeding, ask a doctor before use.

OTC - PREGNANCY OR BREAST FEEDING SECTION

If pregnant or breast-feeding, ask a doctor before use.

OTC - KEEP OUT OF REACH OF CHILDREN SECTION

Keep out of reach of children